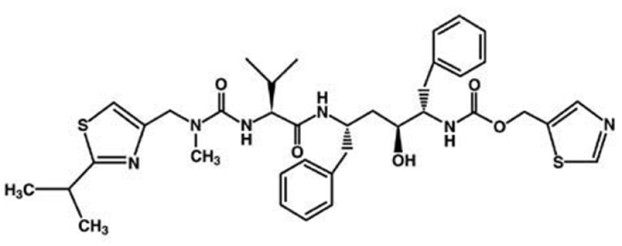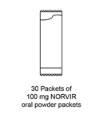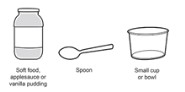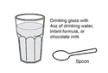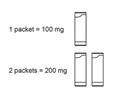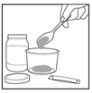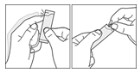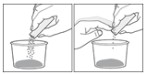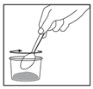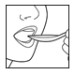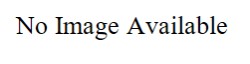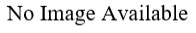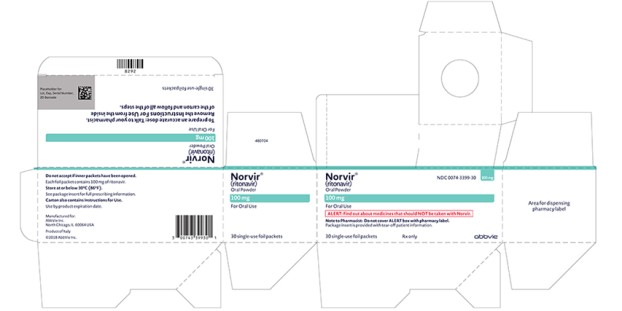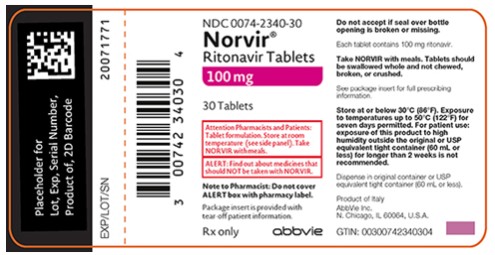 DRUG LABEL: Norvir
NDC: 0074-3333 | Form: TABLET, FILM COATED
Manufacturer: AbbVie Inc.
Category: prescription | Type: HUMAN PRESCRIPTION DRUG LABEL
Date: 20240703

ACTIVE INGREDIENTS: RITONAVIR 100 mg/1 1
INACTIVE INGREDIENTS: COPOVIDONE K25-31; ANHYDROUS DIBASIC CALCIUM PHOSPHATE; SORBITAN MONOLAURATE; SILICON DIOXIDE; SODIUM STEARYL FUMARATE; HYPROMELLOSE, UNSPECIFIED; TITANIUM DIOXIDE; POLYETHYLENE GLYCOL 400; HYDROXYPROPYL CELLULOSE, UNSPECIFIED; TALC; POLYETHYLENE GLYCOL 3350; POLYSORBATE 80

HIGHLIGHTS OF PRESCRIBING INFORMATION

These highlights do not include all the information needed to use NORVIR safely and effectively. See full prescribing information for NORVIR.
NORVIR (ritonavir) tablets, for oral use
NORVIR (ritonavir) oral powder
Initial U.S. Approval: 1996

WARNING: DRUG-DRUG INTERACTIONS LEADING TO POTENTIALLY SERIOUS AND/OR LIFE THREATENING REACTIONS

See full prescribing information for complete boxed warning

Co-administration of NORVIR with several classes of drugs including sedative hypnotics, antiarrhythmics, or ergot alkaloid preparations may result in potentially serious and/or life-threatening adverse events due to possible effects of NORVIR on the hepatic metabolism of certain drugs. Review medications taken by patients prior to prescribing NORVIR or when prescribing other medications to patients already taking NORVIR. (4, 5.1)

1 INDICATIONS AND USAGE

NORVIR tablets are HIV protease inhibitors indicated in combination with other antiretroviral agents for the treatment of HIV-1 infection (1)

NORVIR oral powder is indicated in combination with other antiretroviral agents for the treatment of pediatric patients with HIV-1 infection (1)

2 DOSAGE AND ADMINISTRATION

- Adult patients: 600 mg twice-day with meals (2.2)
- Pediatrics patients: The recommended twice daily dose for children greater than one month of age is based on body surface area and should not exceed 600 mg twice daily with meals (2.3)
- NORVIR oral powder can only be used for dosing increments of 100 mg (2.4)
- Instructions for Use should be followed for preparation and administration of NORVIR oral powder (2.4)
- Dose modification for NORVIR is necessary when used with other protease inhibitors (2.5)

3 DOSAGE FORMS AND STRENGTHS

- Tablet: 100 mg (3)
- Oral Powder: 100 mg per packet (3)

4 CONTRAINDICATIONS

- NORVIR is contraindicated in patients with known hypersensitivity to ritonavir (e.g., toxic epidermal necrolysis, Stevens-Johnson syndrome) or any of its ingredients (4)
- Co-administration with drugs highly dependent on CYP3A for clearance and for which elevated plasma concentrations may be associated with serious and/or life-threatening events (4)
- Co-administration with drugs that significantly reduce ritonavir (4)

5 WARNINGS AND PRECAUTIONS

The following have been observed in patients receiving NORVIR:

- The concomitant use of NORVIR and certain other drugs may result in known or potentially significant drug interactions. Consult the full prescribing information prior to and during treatment for potential drug interactions. (5.1, 7.2)
- Hepatotoxicity: Fatalities have occurred. Monitor liver function before and during therapy, especially in patients with underlying hepatic disease, including hepatitis B and hepatitis C, or marked transaminase elevations (5.2, 8.6)
- Pancreatitis: Fatalities have occurred; suspend therapy as clinically appropriate (5.3)
- Allergic Reactions/Hypersensitivity: Allergic reactions have been reported and include anaphylaxis, toxic epidermal necrolysis, Stevens-Johnson syndrome, bronchospasm and angioedema. Discontinue treatment if severe reactions develop (5.4, 6.2)
- PR interval prolongation may occur in some patients. Cases of second and third degree heart block have been reported. Use with caution with patients with preexisting conduction system disease, ischemic heart disease, cardiomyopathy, underlying structural heart disease or when administering with other drugs that may prolong the PR interval (5.5, 12.3)
- Total cholesterol and triglycerides elevations: Monitor prior to therapy and periodically thereafter (5.6)
- Patients may develop new onset or exacerbations of diabetes mellitus, hyperglycemia (5.7)
- Patients may develop immune reconstitution syndrome (5.8)
- Patients may develop redistribution/accumulation of body fat (5.9)
- Hemophilia: Spontaneous bleeding may occur, and additional factor VIII may be required (5.10)

6 ADVERSE REACTIONS

The most frequently reported adverse drug reactions among patients receiving NORVIR alone or in combination with other antiretroviral drugs were gastrointestinal (including diarrhea, nausea, vomiting, abdominal pain (upper and lower), neurological disturbances (including paresthesia and oral paresthesia), rash, and fatigue/asthenia (6.1)

To report SUSPECTED ADVERSE REACTIONS, contact AbbVie Inc. at 1-800-633-9110 or FDA at 1-800-FDA-1088 or www.fda.gov/medwatch.

7 DRUG INTERACTIONS

- Co-administration of NORVIR can alter the concentrations of other drugs. The potential for drug-drug interactions must be considered prior to and during therapy (4, 5.1, 7, 12.3)

8 USE IN SPECIFIC POPULATIONS

- Lactation: Women infected with HIV should be instructed not to breastfeed due to the potential for HIV transmission (8.2).

FULL PRESCRIBING INFORMATION

WARNING: DRUG-DRUG INTERACTIONS LEADING TO POTENTIALLY SERIOUS AND/OR LIFE THREATENING REACTIONS

Co-administration of NORVIR with several classes of drugs including sedative hypnotics, antiarrhythmics, or ergot alkaloid preparations may result in potentially serious and/or life-threatening adverse events due to possible effects of NORVIR on the hepatic metabolism of certain drugs. Review medications taken by patients prior to prescribing NORVIR or when prescribing other medications to patients already taking NORVIR [see Contraindications (4), Warnings and Precautions (5.1)].

1 INDICATIONS AND USAGE

NORVIR tablets are indicated in combination with other antiretroviral agents for the treatment of HIV-1 infection.

NORVIR oral powder is indicated in combination with other antiretroviral agents for the treatment of pediatric patients with HIV-1 infection.

2 DOSAGE AND ADMINISTRATION

2.1 General Administration Recommendations

- NORVIR must be used in combination with other antiretroviral agents.
- NORVIR is administered orally. NORVIR tablets should be swallowed whole, and not chewed, broken or crushed. Take NORVIR with meals.
- NORVIR oral powder should be mixed with soft food such as apple sauce or vanilla pudding, or mixed with liquid such as water, chocolate milk, or infant formula [see Dosage and Administration (2.4) and Instructions for Use]. The bitter aftertaste of NORVIR oral powder may be lessened if administered with food.

2.2 Dosage Recommendations in Adults

Recommended Dosage for Treatment of HIV-1:

The recommended dosage of NORVIR is 600 mg twice daily by mouth to be taken with meals. Use of a dose titration schedule may help to reduce treatment-emergent adverse events while maintaining appropriate ritonavir plasma levels. NORVIR should be started at no less than 300 mg twice daily and increased at 2 to 3 day intervals by 100 mg twice daily. The maximum dose of 600 mg twice daily should not be exceeded upon completion of the titration [see Dosage and Administration (2.5)].

2.3 Dosage Recommendations in Pediatric Patients

NORVIR must be used in combination with other antiretroviral agents [see Dosage and Administration (2)]. The recommended dosage of NORVIR in pediatric patients older than 1 month is 350 to 400 mg per m^2 twice daily by mouth to be taken with meals and should not exceed 600 mg twice daily. NORVIR should be started at 250 mg per m^2 twice daily and increased at 2 to 3 day intervals by 50 mg per m^2 twice daily. If patients do not tolerate 400 mg per m^2 twice daily due to adverse events, the highest tolerated dose may be used for maintenance therapy in combination with other antiretroviral agents, however, alternative therapy should be considered [see Dosage and Administration (2.5)].

2.4 Preparation of Norvir Oral Powder

For details on the preparation and administration of NORVIR oral powder (see Instructions for Use). NORVIR oral powder should only be used for dosing increments of 100 mg.

Prepare the dose using the required number of packets. For example, use one packet for doses of 100 mg and two packets for doses of 200 mg. Pour and mix the entire contents of each packet over soft food or liquid. All of the powder mixed with soft food or liquid should be administered within 2 hours of preparation. If not administered within 2 hours of preparation, the mixture should be discarded and a new dose prepared.

The prescribed dose of NORVIR oral powder can be administered via a feeding tube after being mixed with water (see Instructions for Use). Follow the instructions for the feeding tube to administer the medicine.

2.5 Dose Modification due to Drug Interaction

Dose reduction of NORVIR is necessary when used with other protease inhibitors: atazanavir, darunavir, fosamprenavir, saquinavir, and tipranavir.

Prescribers should consult the full prescribing information and clinical study information of these protease inhibitors if they are co-administered with a reduced dose of ritonavir [see Warnings and Precautions (5.1), and Drug Interactions (7)].

3 DOSAGE FORMS AND STRENGTHS

- NORVIR Tablets

White film-coated ovaloid tablets debossed with the "a" logo and the code NK providing 100 mg ritonavir.

White film-coated ovaloid tablets debossed with “NK” on one side providing 100 mg ritonavir.

- NORVIR Oral Powder

Beige/pale yellow to yellow powder in child-resistant packet. Each packet contains 100 mg of ritonavir.

4 CONTRAINDICATIONS

- When co-administering NORVIR with other protease inhibitors, see the full prescribing information for that protease inhibitor including contraindication information.
- NORVIR is contraindicated in patients with known hypersensitivity (e.g., toxic epidermal necrolysis (TEN) or Stevens-Johnson syndrome) to ritonavir or any of its ingredients.
- NORVIR is contraindicated with drugs that are highly dependent on CYP3A for clearance and for which elevated plasma concentrations are associated with serious and/or life-threatening reactions [see Drug Interactions (7.1) and Clinical Pharmacology (12.3)].
  ○ Alpha 1- Adrenoreceptor Antagonist : alfuzosin
  ○ Antianginal: ranolazine
  ○ Antiarrhythmics: amiodarone, dronedarone, flecainide, propafenone, quinidine
  ○ Antifungal: voriconazole
  ○ Anti-gout: colchicine
  ○ Antipsychotics: lurasidone, pimozide
  ○ Ergot Derivatives: dihydroergotamine, ergotamine, methylergonovine
  ○ GI Motility Agent: cisapride
  ○ HMG-CoA Reductase Inhibitors: lovastatin, simvastatin
  ○ Microsomal triglyceride transfer protein (MTTP) Inhibitor: lomitapide
  ○ PDE5 Inhibitor: sildenafil (Revatio®) when used for the treatment of pulmonary arterial hypertension
  ○ Sedative/Hypnotics: triazolam, orally administered midazolam
- NORVIR is contraindicated with drugs that are potent CYP3A inducers where significantly reduced ritonavir plasma concentrations may be associated with the potential for loss of virologic response and possible resistance and cross-resistance [see Drug Interactions (7.2) and Clinical Pharmacology (12.3)].
  ○ Anticancer Agents: apalutamide
  ○ Herbal Products: St. John's Wort (hypericum perforatum)

5 WARNINGS AND PRECAUTIONS

5.1 Risk of Serious Adverse Reactions Due to Drug Interactions

Initiation of NORVIR, a CYP3A inhibitor, in patients receiving medications metabolized by CYP3A or initiation of medications metabolized by CYP3A in patients already receiving NORVIR, may increase plasma concentrations of medications metabolized by CYP3A. Initiation of medications that inhibit or induce CYP3A may increase or decrease concentrations of NORVIR, respectively. These interactions may lead to:

- Clinically significant adverse reactions, potentially leading to severe, life-threatening, or fatal events from greater exposures of concomitant medications.
- Clinically significant adverse reactions from greater exposures of NORVIR.
- Loss of therapeutic effect of NORVIR and possible development of resistance.

When co-administering NORVIR with other protease inhibitors, see the full prescribing information for that protease inhibitor including important Warnings and Precautions.

See Table 3 for steps to prevent or manage these possible and known significant drug interactions, including dosing recommendations [see Drug Interactions (7)]. Consider the potential for drug interactions prior to and during NORVIR therapy; review concomitant medications during NORVIR therapy, and monitor for the adverse reactions associated with the concomitant medications [see Contraindications (4) and Drug Interactions (7)].

5.2 Hepatotoxicity

Hepatic transaminase elevations exceeding 5 times the upper limit of normal, clinical hepatitis, and jaundice have occurred in patients receiving NORVIR alone or in combination with other antiretroviral drugs (see Table 2). There may be an increased risk for transaminase elevations in patients with underlying hepatitis B or C. Therefore, caution should be exercised when administering NORVIR to patients with pre-existing liver diseases, liver enzyme abnormalities, or hepatitis. Increased AST/ALT monitoring should be considered in these patients, especially during the first three months of NORVIR treatment [see Use in Specific Populations (8.6)].

There have been postmarketing reports of hepatic dysfunction, including some fatalities. These have generally occurred in patients taking multiple concomitant medications and/or with advanced AIDS.

5.3 Pancreatitis

Pancreatitis has been observed in patients receiving NORVIR therapy, including those who developed hypertriglyceridemia. In some cases fatalities have been observed. Patients with advanced HIV disease may be at increased risk of elevated triglycerides and pancreatitis [see Warnings and Precautions (5.6)]. Pancreatitis should be considered if clinical symptoms (nausea, vomiting, abdominal pain) or abnormalities in laboratory values (such as increased serum lipase or amylase values) suggestive of pancreatitis should occur. Patients who exhibit these signs or symptoms should be evaluated and NORVIR therapy should be discontinued if a diagnosis of pancreatitis is made.

5.4 Allergic Reactions/Hypersensitivity

Allergic reactions including urticaria, mild skin eruptions, bronchospasm, and angioedema have been reported. Cases of anaphylaxis, toxic epidermal necrolysis (TEN), and Stevens-Johnson syndrome have also been reported. Discontinue treatment if severe reactions develop.

5.5 PR Interval Prolongation

Ritonavir prolongs the PR interval in some patients. Post marketing cases of second or third degree atrioventricular block have been reported in patients.

NORVIR should be used with caution in patients with underlying structural heart disease, preexisting conduction system abnormalities, ischemic heart disease, cardiomyopathies, as these patients may be at increased risk for developing cardiac conduction abnormalities.

The impact on the PR interval of co-administration of ritonavir with other drugs that prolong the PR interval (including calcium channel blockers, beta-adrenergic blockers, digoxin and atazanavir) has not been evaluated. As a result, co-administration of ritonavir with these drugs should be undertaken with caution, particularly with those drugs metabolized by CYP3A. Clinical monitoring is recommended [see Drug Interactions (7) and Clinical Pharmacology (12.3)].

5.6 Lipid Disorders

Treatment with NORVIR therapy alone or in combination with saquinavir has resulted in substantial increases in the concentration of total cholesterol and triglycerides [see Adverse Reactions (6.1)]. Triglyceride and cholesterol testing should be performed prior to initiating NORVIR therapy and at periodic intervals during therapy. Lipid disorders should be managed as clinically appropriate, taking into account any potential drug-drug interactions with NORVIR and HMG CoA reductase inhibitors [see Contraindications (4) and Drug Interactions (7)].

5.7 Diabetes Mellitus/Hyperglycemia

New onset diabetes mellitus, exacerbation of pre-existing diabetes mellitus, and hyperglycemia have been reported during postmarketing surveillance in HIV-infected patients receiving protease inhibitor therapy. Some patients required either initiation or dose adjustments of insulin or oral hypoglycemic agents for treatment of these events. In some cases, diabetic ketoacidosis has occurred. In those patients who discontinued protease inhibitor therapy, hyperglycemia persisted in some cases. Because these events have been reported voluntarily during clinical practice, estimates of frequency cannot be made and a causal relationship between protease inhibitor therapy and these events has not been established. Consider monitoring for hyperglycemia, new onset diabetes mellitus, or an exacerbation of diabetes mellitus in patients treated with NORVIR.

5.8 Immune Reconstitution Syndrome

Immune reconstitution syndrome has been reported in HIV-infected patients treated with combination antiretroviral therapy, including NORVIR. During the initial phase of combination antiretroviral treatment, patients whose immune system responds may develop an inflammatory response to indolent or residual opportunistic infections (such as Mycobacterium avium infection, cytomegalovirus, Pneumocystis jiroveci pneumonia, or tuberculosis), which may necessitate further evaluation and treatment.

Autoimmune disorders (such as Graves’ disease, polymyositis, and Guillain-Barré syndrome) have also been reported to occur in the setting of immune reconstitution, however, the time to onset is more variable, and can occur many months after initiation of treatment.

5.9 Fat Redistribution

Redistribution/accumulation of body fat including central obesity, dorsocervical fat enlargement (buffalo hump), peripheral wasting, facial wasting, breast enlargement, and "cushingoid appearance" have been observed in patients receiving antiretroviral therapy. The mechanism and long-term consequences of these events are currently unknown. A causal relationship has not been established.

5.10 Patients with Hemophilia

There have been reports of increased bleeding, including spontaneous skin hematomas and hemarthrosis, in patients with hemophilia type A and B treated with protease inhibitors. In some patients additional factor VIII was given. In more than half of the reported cases, treatment with protease inhibitors was continued or reintroduced. A causal relationship between protease inhibitor therapy and these events has not been established.

5.11 Resistance/Cross-resistance

Varying degrees of cross-resistance among protease inhibitors have been observed. Continued administration of ritonavir 600 mg twice daily following loss of viral suppression may increase the likelihood of cross-resistance to other protease inhibitors [see Microbiology (12.4)].

5.12 Laboratory Tests

Ritonavir has been shown to increase triglycerides, cholesterol, SGOT (AST), SGPT (ALT), GGT, CPK, and uric acid. Appropriate laboratory testing should be performed prior to initiating NORVIR therapy and at periodic intervals or if any clinical signs or symptoms occur during therapy.

6 ADVERSE REACTIONS

The following adverse reactions are discussed in greater detail in other sections of the labeling.

- Drug Interactions [see Warnings and Precautions (5.1)]
- Hepatotoxicity [see Warnings and Precautions (5.2)]
- Pancreatitis [see Warnings and Precautions (5.3)]
- Allergic Reactions/Hypersensitivity [see Warnings and Precautions (5.4)]

When co-administering NORVIR with other protease inhibitors, see the full prescribing information for that protease inhibitor including adverse reactions.

6.1 Clinical Trial Experience

Because clinical trials are conducted under widely varying conditions, adverse reactions rates observed in the clinical trials of a drug cannot be directly compared to rates in the clinical trials of another drug and may not reflect the rates observed in practice.

Adverse Reactions in Adults

The safety of NORVIR alone and in combination with other antiretroviral agents was studied in 1,755 adult patients. Table 1 lists treatment-emergent Adverse Reactions (with possible or probable relationship to study drug) occurring in greater than or equal to 1% of adult patients receiving NORVIR in combined Phase II/IV studies.

The most frequently reported adverse drug reactions among patients receiving NORVIR alone or in combination with other antiretroviral drugs were gastrointestinal (including diarrhea, nausea, vomiting, abdominal pain (upper and lower)), neurological disturbances (including paresthesia and oral paresthesia), rash, and fatigue/asthenia.

Table 1. Treatment-Emergent Adverse Reactions (With Possible or Probable Relationship to Study Drug) Occurring in greater than or equal to 1% of Adult Patients Receiving NORVIR in Combined Phase II/IV Studies (N = 1,755)
Adverse Reactions | n | %
Eye disorders
Blurred vision | 113 | 6.4
Gastrointestinal disorders
Abdominal Pain (upper and lower)* | 464 | 26.4
Diarrhea including severe with electrolyte imbalance* | 1,192 | 67.9
Dyspepsia | 201 | 11.5
Flatulence | 142 | 8.1
Gastrointestinal hemorrhage* | 41 | 2.3
Gastroesophageal reflux disease (GERD) | 19 | 1.1
Nausea | 1,007 | 57.4
Vomiting* | 559 | 31.9
General disorders and administration site conditions
Fatigue including asthenia* | 811 | 46.2
Hepatobiliary disorders
Blood bilirubin increased (including jaundice)* | 25 | 1.4
Hepatitis (including increased AST, ALT, GGT)* | 153 | 8.7
Immune system disorders
Hypersensitivity including urticaria and face edema* | 114 | 8.2
Metabolism and nutrition disorders
Edema and peripheral edema* | 110 | 6.3
Gout* | 24 | 1.4
Hypercholesterolemia* | 52 | 3.0
Hypertriglyceridemia* | 158 | 9.0
Lipodystrophy acquired* | 51 | 2.9
Musculoskeletal and connective tissue disorders
Arthralgia and back pain* | 326 | 18.6
Myopathy/creatine phosphokinase increased* | 66 | 3.8
Myalgia | 156 | 8.9
Nervous system disorders
Dizziness* | 274 | 15.6
Dysgeusia* | 285 | 16.2
Paresthesia (including oral paresthesia)* | 889 | 50.7
Peripheral neuropathy | 178 | 10.1
Syncope* | 58 | 3.3
Psychiatric disorders
Confusion* | 52 | 3.0
Disturbance in attention | 44 | 2.5
Renal and urinary disorders
Increased urination* | 74 | 4.2
Respiratory, thoracic and mediastinal disorders
Coughing* | 380 | 21.7
Oropharyngeal Pain* | 279 | 15.9
Skin and subcutaneous tissue disorders
Acne* | 67 | 3.8
Pruritus* | 214 | 12.2
Rash (includes erythematous and maculopapular)* | 475 | 27.1
Vascular disorders
Flushing, feeling hot* | 232 | 13.2
Hypertension* | 58 | 3.3
Hypotension including orthostatic hypotension* | 30 | 1.7
Peripheral coldness* | 21 | 1.2
* Represents a medical concept including several similar MedDRA PTs

Laboratory Abnormalities in Adults

Table 2 shows the percentage of adult patients who developed marked laboratory abnormalities.

Table 2. Percentage of Adult Patients, by Study and Treatment Group, with Chemistry and Hematology Abnormalities Occurring in greater than 3% of Patients Receiving NORVIR
 |  | Study 245 Naive Patients |  |  | Study 247 Advanced Patients |  | Study 462 PI-Naive Patients
Variable | Limit | NORVIR plus ZDV | NORVIR | ZDV | NORVIR | Placebo | NORVIR plus Saquinavir
Chemistry | High
Cholesterol | > 240 mg/dL | 30.7 | 44.8 | 9.3 | 36.5 | 8.0 | 65.2
CPK | > 1000 IU/L | 9.6 | 12.1 | 11.0 | 9.1 | 6.3 | 9.9
GGT | > 300 IU/L | 1.8 | 5.2 | 1.7 | 19.6 | 11.3 | 9.2
SGOT (AST) | > 180 IU/L | 5.3 | 9.5 | 2.5 | 6.4 | 7.0 | 7.8
SGPT (ALT) | > 215 IU/L | 5.3 | 7.8 | 3.4 | 8.5 | 4.4 | 9.2
Triglycerides | > 800 mg/dL | 9.6 | 17.2 | 3.4 | 33.6 | 9.4 | 23.4
Triglycerides | > 1500 mg/dL | 1.8 | 2.6 | - | 12.6 | 0.4 | 11.3
Triglycerides Fasting | > 1500 mg/dL | 1.5 | 1.3 | - | 9.9 | 0.3 | -
Uric Acid | > 12 mg/dL | - | - | - | 3.8 | 0.2 | 1.4
Hematology | Low
Hematocrit | < 30% | 2.6 | - | 0.8 | 17.3 | 22.0 | 0.7
Hemoglobin | < 8.0 g/dL | 0.9 | - | - | 3.8 | 3.9 | -
Neutrophils | ≤ 0.5 x 10^9/L | - | - | - | 6.0 | 8.3 | -
RBC | < 3.0 x 10^12/L | 1.8 | - | 5.9 | 18.6 | 24.4 | -
WBC | < 2.5 x 10^9/L | - | 0.9 | 6.8 | 36.9 | 59.4 | 3.5
- Indicates no events reported.

Adverse Reactions in Pediatric Patients

NORVIR has been studied in 265 pediatric patients greater than 1 month to 21 years of age. The adverse event profile observed during pediatric clinical trials was similar to that for adult patients.

Vomiting, diarrhea, and skin rash/allergy were the only drug-related clinical adverse events of moderate to severe intensity observed in greater than or equal to 2% of pediatric patients enrolled in NORVIR clinical trials.

Laboratory Abnormalities in Pediatric Patients

The following Grade 3-4 laboratory abnormalities occurred in greater than 3% of pediatric patients who received treatment with NORVIR either alone or in combination with reverse transcriptase inhibitors: neutropenia (9%), hyperamylasemia (7%), thrombocytopenia (5%), anemia (4%), and elevated AST (3%).

6.2 Postmarketing Experience

The following adverse events (not previously mentioned in the labeling) have been reported during post-marketing use of NORVIR. Because these reactions are reported voluntarily from a population of unknown size, it is not possible to reliably estimate their frequency or establish a causal relationship to NORVIR exposure.

Body as a Whole

Dehydration, usually associated with gastrointestinal symptoms, and sometimes resulting in hypotension, syncope, or renal insufficiency has been reported. Syncope, orthostatic hypotension, and renal insufficiency have also been reported without known dehydration.

Co-administration of ritonavir with ergotamine or dihydroergotamine has been associated with acute ergot toxicity characterized by vasospasm and ischemia of the extremities and other tissues including the central nervous system.

Cardiovascular System

First-degree AV block, second-degree AV block, third-degree AV block, right bundle branch block have been reported [see Warnings and Precautions (5.5)].

Cardiac and neurologic events have been reported when ritonavir has been co-administered with disopyramide, mexiletine, nefazodone, fluoxetine, and beta blockers. The possibility of drug interaction cannot be excluded.

Endocrine System

Cushing's syndrome and adrenal suppression have been reported when ritonavir has been co-administered with fluticasone propionate or budesonide.

Nervous System

There have been postmarketing reports of seizure. Also, see Cardiovascular System.

Renal and Urinary Disorders

Nephrolithiasis

Skin and subcutaneous tissue disorders

Toxic epidermal necrolysis (TEN) has been reported.

7 DRUG INTERACTIONS

When co-administering NORVIR with other protease inhibitors (atazanavir, darunavir, fosamprenavir, saquinavir, and tipranavir), see the full prescribing information for that protease inhibitor including important information for drug interactions.

7.1 Potential for NORVIR to Affect Other Drugs

Ritonavir is an inhibitor of cytochrome P450 3A (CYP3A) and may increase plasma concentrations of agents that are primarily metabolized by CYP3A. Agents that are extensively metabolized by CYP3A and have high first pass metabolism appear to be the most susceptible to large increases in AUC (greater than 3-fold) when co-administered with ritonavir. Thus, co-administration of NORVIR with drugs highly dependent on CYP3A for clearance and for which elevated plasma concentrations are associated with serious and/or life-threatening events is contraindicated. Co-administration with other CYP3A substrates may require a dose adjustment or additional monitoring as shown in Table 3.

Ritonavir also inhibits CYP2D6 to a lesser extent. Co-administration of substrates of CYP2D6 with ritonavir could result in increases (up to 2-fold) in the AUC of the other agent, possibly requiring a proportional dosage reduction. Ritonavir also appears to induce CYP3A, CYP1A2, CYP2C9, CYP2C19, and CYP2B6 as well as other enzymes, including glucuronosyl transferase.

These examples are a guide and not considered a comprehensive list of all possible drugs that may interact with ritonavir. The healthcare provider should consult appropriate references for comprehensive information.

7.2 Established and Other Potentially Significant Drug Interactions

Table 3 provides a list of established or potentially clinically significant drug interactions. Alteration in dose or regimen may be recommended based on drug interaction studies or predicted interaction [see Contraindications (4), Warnings and Precautions (5.1), and Clinical Pharmacology (12.3)] for magnitude of interaction.

Table 3. Established and Other Potentially Significant Drug Interactions
Concomitant Drug Class: Drug Name | Effect on Concentration of Ritonavir or Concomitant Drug | Clinical Comment
HIV-Antiviral Agents
HIV-1 Protease Inhibitor: atazanavir darunavir fosamprenavir | ↑ amprenavir ↑ atazanavir ↑ darunavir | See the complete prescribing information for fosamprenavir, atazanavir, darunavir for details on co-administration with ritonavir.
HIV-1 Protease Inhibitor: indinavir | ↑ indinavir | Appropriate doses for this combination, with respect to efficacy and safety, have not been established.
HIV-1 Protease Inhibitor: saquinavir | ↑ saquinavir | See the complete prescribing information for saquinavir for details on co-administration of saquinavir and ritonavir. Saquinavir/ritonavir in combination with rifampin is not recommended due to the risk of severe hepatotoxicity (presenting as increased hepatic transaminases) if the three drugs are given together.
HIV-1 Protease Inhibitor: tipranavir | ↑ tipranavir | See the complete prescribing information for tipranavir for details on co-administration of tipranavir and ritonavir.
Non-Nucleoside Reverse Transcriptase Inhibitor: delavirdine | ↑ ritonavir | Appropriate doses of this combination with respect to safety and efficacy have not been established.
HIV-1 CCR5 – antagonist: maraviroc | ↑ maraviroc | See the complete prescribing information for maraviroc for details on co-administration of maraviroc and ritonavir-containing protease inhibitors.
Integrase Inhibitor: raltegravir | ↓ raltegravir | The effects of ritonavir on raltegravir with ritonavir dosage regimens greater than 100 mg twice daily have not been evaluated, however raltegravir concentrations may be decreased with ritonavir coadministration.
Other Agents
Alpha 1- Adrenoreceptor Antagonist: alfuzosin | ↑ alfuzosin | Contraindicated due to potential hypotension [see Contraindications (4)].
Antianginal: ranolazine | ↑ ranolazine | Contraindicated due to potential for serious and/or life-threatening reactions [see Contraindications (4)].
Analgesics, Narcotic: tramadol, propoxyphene, methadone, fentanyl | ↑ analgesics ↓ methadone ↑ fentanyl | A dose decrease may be needed for these drugs when co-administered with ritonavir. Dosage increase of methadone may be considered. Careful monitoring of therapeutic and adverse effects (including potentially fatal respiratory depression) is recommended when fentanyl is concomitantly administered with NORVIR.
Anesthetic: meperidine | ↓ meperidine/ ↑ normeperidine (metabolite) | Dosage increase and long-term use of meperidine with ritonavir are not recommended due to the increased concentrations of the metabolite normeperidine which has both analgesic activity and CNS stimulant activity (e.g., seizures).
Antiarrhythmics: amiodarone, dronedarone, flecainide, propafenone, quinidine | ↑ antiarrhythmics | Contraindicated due to potential for cardiac arrhythmias [see Contraindications (4)].
Antiarrhythmics: disopyramide, lidocaine, mexiletine | ↑ antiarrhythmics | Caution is warranted and therapeutic concentration monitoring is recommended for antiarrhythmics when co-administered with ritonavir, if available.
Anticancer Agents: abemaciclib, apalutamide, dasatinib, encorafenib, ibrutinib, ivosidenib, neratinib, nilotinib, venetoclax, vinblastine, vincristine | ↑ anticancer agents ↓ ritonavir# | Apalutamide is contraindicated due to potential for loss of virologic response and possible resistance to NORVIR or to the class of protease inhibitors [see Contraindications (4)]. Avoid co-administration of encorafenib or ivosidenib with NORVIR due to potential risk of serious adverse events such as QT interval prolongation. If co-administration of encorafenib with NORVIR cannot be avoided, modify dose as recommended in encorafenib USPI. If co-administration of ivosidenib with NORVIR cannot be avoided, reduce ivosidenib dose to 250 mg once daily. Avoid use of neratinib, venetoclax or ibrutinib with NORVIR. For vincristine and vinblastine, consideration should be given to temporarily withholding the ritonavir containing antiretroviral regimen in patients who develop significant hematologic or gastrointestinal side effects when ritonavir is administered concurrently with vincristine or vinblastine. Clinicians should be aware that if the ritonavir containing regimen is withheld for a prolonged period, consideration should be given to altering the regimen to not include a CYP3A or P-gp inhibitor in order to control HIV-1 viral load. A decrease in the dosage or an adjustment of the dosing interval of nilotinib and dasatinib may be necessary for patients requiring co-administration with strong CYP3A inhibitors such as NORVIR. Please refer to the nilotinib and dasatinib prescribing information for dosing instructions.
Anticoagulant: warfarin | ↑↓ warfarin | Initial frequent monitoring of the INR during ritonavir and warfarin co-administration is recommended.
Anticoagulant: rivaroxaban | ↑ rivaroxaban | Avoid concomitant use of rivaroxaban and ritonavir. Co-administration of ritonavir and rivaroxaban may lead to risk of increased bleeding.
Anticonvulsants: carbamazepine, clonazepam, ethosuximide | ↑ anticonvulsants | A dose decrease may be needed for these drugs when co-administered with ritonavir and therapeutic concentration monitoring is recommended for these anticonvulsants, if available.
Anticonvulsants: divalproex, lamotrigine, phenytoin | ↓ anticonvulsants | A dose increase may be needed for these drugs when co-administered with ritonavir and therapeutic concentration monitoring is recommended for these anticonvulsants, if available.
Antidepressants: nefazodone, selective serotonin reuptake inhibitors (SSRIs): e.g. fluoxetine, paroxetine, tricyclics: e.g. amitriptyline, nortriptyline | ↑ antidepressants | A dose decrease may be needed for these drugs when co-administered with ritonavir.
Antidepressant: bupropion | ↓ bupropion ↓ active metabolite, hydroxybupropion | Patients receiving ritonavir and bupropion concurrently should be monitored for an adequate clinical response to bupropion.
Antidepressant: desipramine | ↑ desipramine | Dosage reduction and concentration monitoring of desipramine is recommended.
Antidepressant: trazodone | ↑ trazodone | Adverse events of nausea, dizziness, hypotension and syncope have been observed following co-administration of trazodone and NORVIR. A lower dose of trazodone should be considered.
Antiemetic: dronabinol | ↑ dronabinol | A dose decrease of dronabinol may be needed when co-administered with ritonavir.
Antifungals: ketoconazole itraconazole voriconazole | ↑ ketoconazole ↑ itraconazole ↓ voriconazole | High doses of ketoconazole or itraconazole (greater than 200 mg per day) are not recommended. Co-administration of voriconazole and ritonavir doses of 400 mg every 12 hours or greater is contraindicated due to the potential for loss of antifungal response [see Contraindications (4)]. Co-administration of voriconazole and ritonavir 100 mg should be avoided, unless an assessment of the benefit/risk to the patient justifies the use of voriconazole.
Anti-gout: colchicine | ↑ colchicine | Contraindicated due to potential for serious and/or life-threatening reactions in patients with renal and/or hepatic impairment [see Contraindications (4)]. For patients with normal renal or hepatic function: Treatment of gout flares-co-administration of colchicine in patients on ritonavir:0.6 mg (one tablet) for one dose, followed by 0.3 mg (half tablet) one hour later. Dose to be repeated no earlier than three days. Prophylaxis of gout flares-co-administration of colchicine in patients on ritonavir: If the original colchicine regimen was 0.6 mg twice a day, the regimen should be adjusted to 0.3 mg once a day.If the original colchicine regimen was 0.6 mg once a day, the regimen should be adjusted to 0.3 mg once every other day. Treatment of familial Mediterranean fever (FMF)-co-administration of colchicine in patients on ritonavir: Maximum daily dose of 0.6 mg (may be given as 0.3 mg twice a day).
Anti-infective: clarithromycin | ↑ clarithromycin | For patients with renal impairment, adjust clarithromycin dose as follows:; - For patients with CLCR 30 to 60 mL per min the dose of clarithromycin should be reduced by 50%. - For patients with CLCR less than 30 mL per min the dose of clarithromycin should be decreased by 75%.; No dose adjustment for patients with normal renal function is necessary.
Antimycobacterial: bedaquiline | ↑ bedaquiline | Bedaquiline should only be used with ritonavir if the benefit of co-administration outweighs the risk.
Antimycobacterial: rifabutin | ↑ rifabutin and rifabutin metabolite | Dosage reduction of rifabutin by at least three-quarters of the usual dose of 300 mg per day is recommended (e.g., 150 mg every other day or three times a week). Further dosage reduction may be necessary.
Antimycobacterial: rifampin | ↓ ritonavir | May lead to loss of virologic response. Alternate antimycobacterial agents such as rifabutin should be considered.
Antiparasitic: atovaquone | ↓ atovaquone | Clinical significance is unknown; however, increase in atovaquone dose may be needed.
Antiparasitic: quinine | ↑ quinine | A dose decrease of quinine may be needed when co-administered with ritonavir.
Antipsychotics: lurasidone pimozide | ↑ lurasidone ↑ pimozide | Contraindicated due to potential for serious and/or life-threatening reactions [see Contraindications (4)]. Contraindicated due to potential for serious and/or life-threatening reactions such as cardiac arrhythmias [see Contraindications (4)].
Antipsychotics: perphenazine, risperidone, thioridazine | ↑ antipsychotics | A dose decrease may be needed for these drugs when co-administered with ritonavir.
Antipsychotics: quetiapine | ↑ quetiapine | Initiation of NORVIR in patients taking quetiapine: Consider alternative antiretroviral therapy to avoid increases in quetiapine exposures. If coadministration is necessary, reduce the quetiapine dose to 1/6 of the current dose and monitor for quetiapine-associated adverse reactions. Refer to the quetiapine prescribing information for recommendations on adverse reaction monitoring. Initiation of quetiapine in patients taking NORVIR: Refer to the quetiapine prescribing information for initial dosing and titration of quetiapine.
β-Blockers: metoprolol, timolol | ↑ beta-blockers | Caution is warranted and clinical monitoring of patients is recommended. A dose decrease may be needed for these drugs when co-administered with ritonavir.
Bronchodilator: theophylline | ↓ theophylline | Increased dosage of theophylline may be required; therapeutic monitoring should be considered.
Calcium channel blockers: diltiazem, nifedipine, verapamil | ↑ calcium channel blockers | Caution is warranted and clinical monitoring of patients is recommended. A dose decrease may be needed for these drugs when co-administered with ritonavir.
Digoxin | ↑ digoxin | Concomitant administration of ritonavir with digoxin may increase digoxin levels. Caution should be exercised when co-administering ritonavir with digoxin, with appropriate monitoring of serum digoxin levels.
Endothelin receptor antagonists: bosentan | ↑ bosentan | Co-administration of bosentan in patients on ritonavir: In patients who have been receiving ritonavir for at least 10 days, start bosentan at 62.5 mg once daily or every other day based upon individual tolerability. Co-administration of ritonavir in patients on bosentan: Discontinue use of bosentan at least 36 hours prior to initiation of ritonavir. After at least 10 days following the initiation of ritonavir, resume bosentan at 62.5 mg once daily or every other day based upon individual tolerability.
GnRH Receptor Antagonists: elagolix | ↑ elagolix ↓ ritonavir | Concomitant use of elagolix 200 mg twice daily and NORVIR for more than 1 month is not recommended due to potential risk of adverse events such as bone loss and hepatic transaminase elevations. Limit concomitant use of elagolix 150 mg once daily and NORVIR to 6 months.
Ergot Derivatives: dihydroergotamine, ergotamine, methylergonovine | ↑ ergot derivatives | Contraindicated due to potential for acute ergot toxicity characterized by vasospasm and ischemia of the extremities and other tissues including the central nervous system [see Contraindications (4)].
GI Motility Agent: cisapride | ↑ cisapride | Contraindicated due to potential for cardiac arrhythmias [see Contraindications (4)].
Hepatitis C direct acting antiviral: glecaprevir/pibrentasvir simeprevir | ↑ glecaprevir ↑ pibrentasvir ↑simeprevir | It is not recommended to co-administer ritonavir with glecaprevir/pibrentasvir, or simeprevir.
Herbal Products: St. John's Wort (hypericum perforatum) | ↓ ritonavir | Contraindicated due to potential for loss of virologic response and possible resistance to NORVIR or to the class of protease inhibitors [see Contraindications (4)].
Lipid-modifying agents HMG-CoA Reductase Inhibitor: lovastatin simvastatin atorvastatin rosuvastatin Microsomal triglyceride transfer protein (MTTP) Inhibitor: lomitapide | ↑ lovastatin ↑ simvastatin ↑ atorvastatin ↑ rosuvastatin ↑ lomitapide | Contraindicated due to potential for myopathy including rhabdomyolysis [see Contraindications (4)]. Titrate atorvastatin and rosuvastatin dose carefully and use the lowest necessary dose.If NORVIR is used with another protease inhibitor, see the complete prescribing information for the concomitant protease inhibitor for details on co-administration with atorvastatin and rosuvastatin. Lomitapide is a sensitive substrate for CYP3A4 metabolism. CYP3A4 inhibitors increase the exposure of lomitapide, with strong inhibitors increasing exposure approximately 27-fold. Concomitant use of moderate or strong CYP3A4 inhibitors with lomitapide is contraindicated due to potential for hepatotoxicity [see Contraindications (4)].
Immunosuppressants: cyclosporine, tacrolimus, sirolimus (rapamycin) | ↑ immunosuppressants | Therapeutic concentration monitoring is recommended for immunosuppressant agents when co-administered with ritonavir.
Kinase Inhibitors: fostamatinib (also see anticancer agents above) | ↑ fostamatinib metabolite R406 | Monitor for toxicities of R406 exposure resulting in dose-related adverse events such as hepatotoxicity and neutropenia. Fostamatinib dose reduction may be required.
Long-acting beta-adrenoceptor agonist: salmeterol | ↑ salmeterol | Concurrent administration of salmeterol and ritonavir is not recommended. The combination may result in increased risk of cardiovascular adverse events associated with salmeterol, including QT prolongation, palpitations and sinus tachycardia.
Oral Contraceptives or Patch Contraceptives: ethinyl estradiol | ↓ ethinyl estradiol | Alternate methods of contraception should be considered.
PDE5 Inhibitors: avanafil sildenafil, tadalafil, vardenafil | ↑ avanafil ↑ sildenafil ↑ tadalafil ↑ vardenafil | Sildenafil when used for the treatment of pulmonary arterial hypertension (Revatio®) is contraindicated due to the potential for sildenafil-associated adverse events, including visual abnormalities, hypotension, prolonged erection, and syncope [see Contraindications (4)]. Do not use ritonavir with avanafil because a safe and effective avanafil dosage regimen has not been established. Particular caution should be used when prescribing sildenafil, tadalafil or vardenafil in patients receiving ritonavir. Coadministration of ritonavir with these drugs may result in an increase in PDE5 inhibitor associated adverse events, including hypotension, syncope, visual changes, and prolonged erection. Use of PDE5 inhibitors for pulmonary arterial hypertension (PAH): Sildenafil (Revatio®) is contraindicated [see Contraindications (4)]. The following dose adjustments are recommended for use of tadalafil (Adcirca®) with ritonavir: Co-administration of ADCIRCA in patients on ritonavir: In patients receiving ritonavir for at least one week, start ADCIRCA at 20 mg once daily. Increase to 40 mg once daily based upon individual tolerability. Co-administration of ritonavir in patients on ADCIRCA: Avoid use of ADCIRCA during the initiation of ritonavir. Stop ADCIRCA at least 24 hours prior to starting ritonavir. After at least one week following the initiation of ritonavir, resume ADCIRCA at 20 mg once daily. Increase to 40 mg once daily based upon individual tolerability. Use of PDE5 inhibitors for the treatment of erectile dysfunction: It is recommended not to exceed the following doses:; - Sildenafil: 25 mg every 48 hours - Tadalafil: 10 mg every 72 hours - Vardenafil: 2.5 mg every 72 hours; Use with increased monitoring for adverse events.
Sedative/hypnotics: buspirone, clorazepate, diazepam, estazolam, flurazepam, zolpidem | ↑ sedative/hypnotics | A dose decrease may be needed for these drugs when co-administered with ritonavir.
Sedative/Hypnotics: triazolam, orally administered midazolam | ↑ triazolam ↑ midazolam | Contraindicated due to potential for prolonged or increased sedation or respiratory depression [see Contraindications (4)].
Sedative/hypnotics: Parenteral midazolam | ↑ midazolam | Co-administration should be done in a setting which ensures close clinical monitoring and appropriate medical management in case of respiratory depression and/or prolonged sedation. Dosage reduction for midazolam should be considered, especially if more than a single dose of midazolam is administered.
Stimulant: methamphetamine | ↑ methamphetamine | Use with caution. A dose decrease of methamphetamine may be needed when co-administered with ritonavir.
Systemic/Inhaled/ Nasal/Ophthalmic Corticosteroids: e.g., betamethasone budesonide ciclesonide dexamethasone fluticasone methylprednisolone mometasone prednisone triamcinolone | ↑ glucocorticoids | Coadministration with corticosteroids whose exposures are significantly increased by strong CYP3A inhibitors can increase the risk for Cushing’s syndrome and adrenal suppression.Alternative corticosteroids including beclomethasone and prednisolone (whose PK and/or PD are less affected by strong CYP3A inhibitors relative to other studied steroids) should be considered, particularly for long-term use.
# refers to interaction with apalutamide.

8 USE IN SPECIFIC POPULATIONS

When co-administering NORVIR with other protease inhibitors, see the full prescribing information for the co-administered protease inhibitor including important information for use in special populations.

8.1 Pregnancy

Pregnancy Exposure Registry

There is a pregnancy exposure registry that monitors pregnancy outcomes in women exposed to NORVIR during pregnancy. Healthcare providers are encouraged to register patients by calling the Antiretroviral Pregnancy Registry (APR) at 1-800-258-4263.

Risk Summary

Prospective pregnancy data from the Antiretroviral Pregnancy Registry (APR) are not sufficient to adequately assess the risk of birth defects or miscarriage. Available data from the APR show no difference in the rate of overall birth defects for ritonavir compared to the background rate for major birth defects of 2.7% in the U.S. reference population of the Metropolitan Atlanta Congenital Defects Program (MACDP) [see Data].

In animal reproduction studies, no evidence of adverse developmental outcomes was observed with oral administration of ritonavir to pregnant rats and rabbits. During organogenesis in the rat and rabbit, systemic exposure (AUC) was approximately 1/3 lower than human exposure at the recommended daily dose. In the rat pre- and post-natal developmental study, maternal systemic exposure to ritonavir was approximately 1/2 of the exposure in humans at the recommended daily dose, based on a body surface area conversion factor [see Data].

The background risk of major birth defects and miscarriage for the indicated population is unknown. All pregnancies have a background risk of birth defect, loss, or other adverse outcomes. In the U.S. general population, the estimated background risk of major birth defects and miscarriage in clinically recognized pregnancies is 2-4% and 15-20%, respectively.

Data

Human Data

Based on prospective reports to the APR of approximately 6100 live births following exposure to ritonavir-containing regimens (including over 2800 live births exposed in the first trimester and over 3200 live births exposed in the second and third trimesters), there was no difference in the rate of overall birth defects for ritonavir compared with the background birth defect rate of 2.7% in the U.S. reference population of the MACDP. The prevalence of birth defects in live births was 2.3% (95% CI: 1.7%-2.9%) following first-trimester exposure to ritonavir-containing regimens and 2.9% (95% CI: 2.3%-3.5%) following second and third trimester exposure to ritonavir-containing regimens.

While placental transfer of ritonavir and fetal ritonavir concentrations are generally low, detectable levels have been observed in cord blood samples and neonate hair.

Animal Data

Ritonavir was administered orally to pregnant rats (at 0, 15, 35, and 75 mg/kg/day) and rabbits (at 0, 25, 50, and 110 mg/kg/day) during organogenesis (on gestation days 6 through 17 and 6 through 19, respectively). No evidence of teratogenicity due to ritonavir was observed in rats and rabbits at doses producing systemic exposures (AUC) equivalent to approximately 1/3 lower than human exposure at the recommended daily dose. Developmental toxicity observed in rats (early resorptions, decreased fetal body weight and ossification delays and developmental variations) occurred at a maternally toxic dose, at an exposure equivalent to approximately 1/3 lower than human exposure at the recommended daily dose. A slight increase in the incidence of cryptorchidism was also noted in rats (at a maternally toxic dose) at an exposure approximately 1/5 lower than human exposure at the recommended daily dose. Developmental toxicity was observed in rabbits (resorptions, decreased litter size and decreased fetal weights) at maternally toxic doses approximately 1.8 times higher than the recommended daily dose, based on a body surface area conversion factor. In pre-and postnatal development study in rats, ritonavir was administered at doses of 0, 15, 35, and 60 mg/kg/day from gestation day 6 through postnatal day 20. At doses of 60 mg/kg/day, no developmental toxicity was noted with ritonavir dosage equivalent to 1/2 of the recommended daily dose, based on a body surface area conversion factor.

8.2 Lactation

Risk Summary

The Centers for Disease Control and Prevention recommend that HIV-infected mothers not breastfeed their infants to avoid risking postnatal transmission of HIV.

Limited published data reports that ritonavir is present in human milk.

There is no information on the effects of ritonavir on the breastfed infant or the effects of the drug on milk production. Because of the potential for (1) HIV transmission (in HIV-negative infants), (2) developing viral resistance (in HIV-positive infants) and (3) serious adverse reactions in a breastfed infant, instruct mothers not to breastfeed if they are receiving NORVIR.

8.3 Females and Males of Reproductive Potential

Contraception

Use of NORVIR may reduce the efficacy of combined hormonal contraceptives. Advise patients using combined hormonal contraceptives to use an effective alternative contraceptive method or an additional barrier method of contraception [see Drug Interactions (7.2)].

8.4 Pediatric Use

In HIV-infected patients age greater than 1 month to 21 years, the antiviral activity and adverse event profile seen during clinical trials and through postmarketing experience were similar to that for adult patients.

8.5 Geriatric Use

Clinical studies of NORVIR did not include sufficient numbers of subjects aged 65 and over to determine whether they respond differently from younger subjects. In general, dose selection for an elderly patient should be cautious, usually starting at the low end of the dosing range, reflecting the greater frequency of decreased hepatic, renal or cardiac function, and of concomitant disease or other drug therapy.

8.6 Hepatic Impairment

No dose adjustment of ritonavir is necessary for patients with either mild (Child-Pugh Class A) or moderate (Child-Pugh Class B) hepatic impairment. No pharmacokinetic or safety data are available regarding the use of ritonavir in subjects with severe hepatic impairment (Child-Pugh Class C), therefore, ritonavir is not recommended for use in patients with severe hepatic impairment [see Warnings and Precautions (5.2), Clinical Pharmacology (12.3)].

10 OVERDOSAGE

Acute Overdosage - Human Overdose Experience

Human experience of acute overdose with NORVIR is limited. One patient in clinical trials took NORVIR 1500 mg per day for two days. The patient reported paresthesias which resolved after the dose was decreased. A post-marketing case of renal failure with eosinophilia has been reported with ritonavir overdose.

The approximate lethal dose was found to be greater than 20 times the related human dose in rats and 10 times the related human dose in mice.

Management of Overdosage

Treatment of overdose with NORVIR consists of general supportive measures including monitoring of vital signs and observation of the clinical status of the patient. There is no specific antidote for overdose with NORVIR. If indicated, elimination of unabsorbed drug should be achieved by gastric lavage; usual precautions should be observed to maintain the airway. Administration of activated charcoal may also be used to aid in removal of unabsorbed drug. Since ritonavir is extensively metabolized by the liver and is highly protein bound, dialysis is unlikely to be beneficial in significant removal of the drug. A Certified Poison Control Center should be consulted for up-to-date information on the management of overdose with NORVIR.

11 DESCRIPTION

NORVIR (ritonavir) is an inhibitor of HIV protease with activity against the Human Immunodeficiency Virus (HIV).

Ritonavir is chemically designated as 10-Hydroxy-2-methyl-5-(1-methylethyl)-1- [2-(1-methylethyl)-4-thiazolyl]-3,6-dioxo-8,11-bis(phenylmethyl)-2,4,7,12- tetraazatridecan-13-oic acid, 5-thiazolylmethyl ester, [5S-(5R*,8R*,10R*,11R*)]. Its molecular formula is C37H48N6O5S2, and its molecular weight is 720.95. Ritonavir has the following structural formula:

Ritonavir is a white-to-light-tan powder. Ritonavir has a bitter metallic taste. It is freely soluble in methanol and ethanol, soluble in isopropanol and practically insoluble in water.

NORVIR tablets are available for oral administration in a strength of 100 mg ritonavir with the following inactive ingredients: copovidone, anhydrous dibasic calcium phosphate, sorbitan monolaurate, colloidal silicon dioxide, and sodium stearyl fumarate. The following are the ingredients in the film coating: hypromellose, titanium dioxide, polyethylene glycol 400, hydroxypropyl cellulose, talc, polyethylene glycol 3350, colloidal silicon dioxide, and polysorbate 80.

NORVIR oral powder is beige/pale yellow to yellow and is available for oral administration as a packet containing 100 mg of ritonavir with the following inactive ingredients: copovidone, sorbitan monolaurate, and colloidal silicon dioxide.

12 CLINICAL PHARMACOLOGY

12.1 Mechanism of Action

Ritonavir is an antiretroviral drug [see Microbiology (12.4)].

12.2 Pharmacodynamics

Cardiac Electrophysiology

QTcF interval was evaluated in a randomized, placebo and active (moxifloxacin 400 mg once-daily) controlled crossover study in 45 healthy adults, with 10 measurements over 12 hours on Day 3. The maximum mean (95% upper confidence bound) time-matched difference in QTcF from placebo after baseline correction was 5.5 (7.6) milliseconds (msec) for 400 mg twice-daily ritonavir. Ritonavir 400 mg twice daily resulted in Day 3 ritonavir exposure that was approximately 1.5 fold higher than observed with ritonavir 600 mg twice-daily dose at steady state.

PR interval prolongation was also noted in subjects receiving ritonavir in the same study on Day 3. The maximum mean (95% confidence interval) difference from placebo in the PR interval after baseline correction was 22 (25) msec for 400 mg twice-daily ritonavir [see Warnings and Precautions (5.6)].

12.3 Pharmacokinetics

The pharmacokinetics of ritonavir have been studied in healthy volunteers and HIV-infected patients (CD4 greater than or equal to 50 cells per μL). See Table 4 for ritonavir pharmacokinetic characteristics.

Absorption

The absolute bioavailability of ritonavir has not been determined. After a 100 mg tablet dose of NORVIR, peak concentrations of ritonavir were achieved approximately 3 hours and 4 hours after dosing under fasting conditions and moderate-fat (857 KCal; 31% fat, 13% protein, and 56% carbohydrate) meal, respectively.

After administration of a single 100 mg dose under fed conditions (approximately 600 Kcal, 30% calories from fat), NORVIR oral powder showed 23% higher exposure compared to the tablet.

Effect of Food on Oral Absorption

The bioavailability of NORVIR tablet and oral powder is decreased under fed conditions as compared to fasted conditions.

Following the administration of a 100 mg tablet dose of NORVIR, Cmax and AUCinf of ritonavir were decreased by 21-23% under moderate fat (857 Kcal, 30% from fat) or high fat conditions (917 Kcal, 60% calories from fat) relative to fasting conditions.

Following the administration of a 100 mg dose of NORVIR oral powder, Cmax and AUCinf of ritonavir were decreased by 23-49% under moderate fat (617 Kcal, 29% calories from fat) or high fat conditions (917 Kcal, 60% calories from fat) relative to fasting conditions.

Metabolism

Nearly all of the plasma radioactivity after a single oral 600 mg dose of ^14C-ritonavir oral solution (n = 5) was attributed to unchanged ritonavir. Five ritonavir metabolites have been identified in human urine and feces. The isopropylthiazole oxidation metabolite (M-2) is the major metabolite and has antiviral activity similar to that of parent drug; however, the concentrations of this metabolite in plasma are low. In vitro studies utilizing human liver microsomes have demonstrated that cytochrome P450 3A (CYP3A) is the major isoform involved in ritonavir metabolism, although CYP2D6 also contributes to the formation of M–2.

Elimination

In a study of five subjects receiving a 600 mg dose of ^14C-ritonavir oral solution, 11.3 ± 2.8% of the dose was excreted into the urine, with 3.5 ± 1.8% of the dose excreted as unchanged parent drug. In that study, 86.4 ± 2.9% of the dose was excreted in the feces with 33.8 ± 10.8% of the dose excreted as unchanged parent drug. Upon multiple dosing, ritonavir accumulation is less than predicted from a single dose possibly due to a time and dose-related increase in clearance.

Table 4. Ritonavir Pharmacokinetic Characteristics
Parameter | N | Values (Mean ± SD)
Vβ/F‡ | 91 | 0.41 ± 0.25 L/kg
t½ |  | 3 - 5 h
CL/F SS† | 10 | 8.8 ± 3.2 L/h
CL/F‡ | 91 | 4.6 ± 1.6 L/h
CLR | 62 | < 0.1 L/h
RBC/Plasma Ratio |  | 0.14
Percent Bound* |  | 98 to 99%
† SS = steady state; patients taking ritonavir 600 mg q12h.
‡ Single ritonavir 600 mg dose.
* Primarily bound to human serum albumin and alpha-1 acid glycoprotein over the ritonavir concentration range of 0.01 to 30 µg/mL.

Special Populations

Gender, Race and Age

No age-related pharmacokinetic differences have been observed in adult patients (18 to 63 years). Ritonavir pharmacokinetics have not been studied in older patients.

A study of ritonavir pharmacokinetics in healthy males and females showed no statistically significant differences in the pharmacokinetics of ritonavir. Pharmacokinetic differences due to race have not been identified.

Pediatric Patients

Steady-state pharmacokinetics were evaluated in 37 HIV-infected patients ages 2 to 14 years receiving doses ranging from 250 mg per m^2 twice-daily to 400 mg per m^2 twice-daily in PACTG Study 310, and in 41 HIV-infected patients ages 1 month to 2 years at doses of 350 and 450 mg per m^2 twice-daily in PACTG Study 345. Across dose groups, ritonavir steady-state oral clearance (CL/F/m^2) was approximately 1.5 to 1.7 times faster in pediatric patients than in adult subjects. Ritonavir concentrations obtained after 350 to 400 mg per m^2 twice-daily in pediatric patients greater than 2 years were comparable to those obtained in adults receiving 600 mg (approximately 330 mg per m^2) twice-daily. The following observations were seen regarding ritonavir concentrations after administration with 350 or 450 mg per m^2 twice-daily in children less than 2 years of age. Higher ritonavir exposures were not evident with 450 mg per m^2 twice-daily compared to the 350 mg per m^2 twice-daily. Ritonavir trough concentrations were somewhat lower than those obtained in adults receiving 600 mg twice-daily. The area under the ritonavir plasma concentration time curve and trough concentrations obtained after administration with 350 or 450 mg per m^2 twice-daily in children less than 2 years were approximately 16% and 60% lower, respectively, than that obtained in adults receiving 600 mg twice daily.

Renal Impairment

Ritonavir pharmacokinetics have not been studied in patients with renal impairment, however, since renal clearance is negligible, a decrease in total body clearance is not expected in patients with renal impairment.

Hepatic Impairment

Dose-normalized steady-state ritonavir concentrations in subjects with mild hepatic impairment (400 mg twice-daily, n = 6) were similar to those in control subjects dosed with 500 mg twice-daily. Dose-normalized steady-state ritonavir exposures in subjects with moderate hepatic impairment (400 mg twice-daily, n= 6) were about 40% lower than those in subjects with normal hepatic function (500 mg twice-daily, n = 6). Protein binding of ritonavir was not statistically significantly affected by mild or moderately impaired hepatic function. No dose adjustment is recommended in patients with mild or moderate hepatic impairment. However, health care providers should be aware of the potential for lower ritonavir concentrations in patients with moderate hepatic impairment and should monitor patient response carefully. Ritonavir has not been studied in patients with severe hepatic impairment.

Pregnancy

Based on evaluation of the published literature, ritonavir exposures are reduced during pregnancy relative to postpartum.

Drug Interactions

[see also Contraindications (4), Warnings and Precautions (5.1), and Drug Interactions (7)]

Table 5 and Table 6 summarize the effects on AUC and Cmax, with 95% confidence intervals (95% CI), of co-administration of ritonavir with a variety of drugs. For information about clinical recommendations see Table 3 in Drug Interactions (7).

Table 5. Drug Interactions - Pharmacokinetic Parameters for Ritonavir in the Presence of the Co-administered Drug
Co- administered Drug | Dose of Co- administered Drug (mg) | Dose of NORVIR (mg) | N | AUC % (95% CI) | Cmax (95% CI) | Cmin (95% CI)
Clarithromycin | 500 q12h, 4 d | 200 q8h, 4 d | 22 | ↑ 12% (2, 23%) | ↑ 15% (2, 28%) | ↑ 14% (-3, 36%)
Didanosine | 200 q12h, 4 d | 600 q12h, 4 d | 12 | ↔ | ↔ | ↔
Fluconazole | 400 single dose, day 1; 200 daily, 4 d | 200 q6h, 4 d | 8 | ↑ 12% (5, 20%) | ↑ 15% (7, 22%) | ↑ 14% (0, 26%)
Fluoxetine | 30 q12h, 8 d | 600 single dose, 1 d | 16 | ↑ 19% (7, 34%) | ↔ | ND
Ketoconazole | 200 daily, 7 d | 500 q12h, 10 d | 12 | ↑ 18% (-3, 52%) | ↑ 10% (-11, 36%) | ND
Rifampin | 600 or 300 daily, 10 d | 500 q12h, 20 d | 7, 9* | ↓ 35% (7, 55%) | ↓ 25% (-5, 46%) | ↓ 49% (-14, 91%)
Voriconazole | 400 q12h, 1 d; then 200 q12h, 8 d | 400 q12h, 9 d |  | ↔ | ↔ | ND
Zidovudine | 200 q8h, 4 d | 300 q6h, 4 d | 10 | ↔ | ↔ | ↔
ND=not determined

Table 6. Drug Interactions - Pharmacokinetic Parameters for Co-administered Drug in the Presence of NORVIR
Co-administered Drug | Dose of Co-administered Drug (mg) | Dose of NORVIR (mg) | N | AUC % (95% CI) | Cmax (95% CI) | Cmin (95% CI)
Alprazolam | 1, single dose | 500 q12h, 10 d | 12 | ↓ 12% (-5, 30%) | ↓ 16% (5, 27%) | ND
Avanafil | 50, single dose | 600 q12h | 14^6 | ↑ 13-fold | ↑ 2.4-fold | ND
Clarithromycin 14-OH clarithromycin metabolite | 500 q12h, 4 d | 200 q8h, 4 d | 22 | ↑ 77% (56, 103%) ↓ 100% | ↑ 31% (15, 51%) ↓ 99% | ↑ 2.8-fold (2.4, 3.3X) ↓ 100%
Desipramine 2-OH desipramine metabolite | 100, single dose | 500 q12h, 12 d | 14 | ↑ 145% (103, 211%) ↓ 15% (3, 26%) | ↑ 22% (12, 35%) ↓ 67% (62, 72%) | ND ND
Didanosine | 200 q12h, 4 d | 600 q12h, 4 d | 12 | ↓ 13% (0, 23%) | ↓ 16% (5, 26%) | ↔
Ethinyl estradiol | 50 µg single dose | 500 q12h, 16 d | 23 | ↓ 40% (31, 49%) | ↓ 32% (24, 39%) | ND
Fluticasone propionate aqueous nasal spray | 200 mcg qd, 7 d | 100 mg q12h, 7 d | 18 | ↑ approximately 350-fold^5 | ↑ approximately 25-fold^5
Indinavir^1 Day 14 Day 15 | 400 q12h, 15 d | 400 q12h, 15 d | 10 | ↑ 6% (-14, 29%) ↓ 7% (-22, 28%) | ↓ 51% (40, 61%) ↓ 62% (52, 70%) | ↑ 4-fold (2.8, 6.8X) ↑ 4-fold (2.5, 6.5X)
Ketoconazole | 200 daily, 7 d | 500 q12h, 10 d | 12 | ↑ 3.4-fold (2.8, 4.3X) | ↑ 55% (40, 72%) | ND
Meperidine Normeperidine metabolite | 50 oral single dose | 500 q12h, 10 d | 8 6 | ↓ 62% (59, 65%) ↑ 47% (-24, 345%) | ↓ 59% (42, 72%) ↑ 87% (42, 147%) | ND ND
Methadone^2 | 5, single dose | 500 q12h, 15 d | 11 | ↓ 36% (16, 52%) | ↓ 38% (28, 46%) | ND
Raltegravir | 400, single dose | 100 q12h, 16 d | 10 | ↓ 16% (-30, 1%) | ↓ 24% (-45, 4%) | ↓ 1% (-30, 40%)
Rivaroxaban | 10, single dose (days 0 and 7) | 600 q12h (days 2 to 7) | 12 | ↑ 150% (130-170%)^7 | ↑ 60% (40-70%)^7 | ND
Rifabutin 25-O-desacetyl rifabutin metabolite | 150 daily, 16 d | 500 q12h, 10 d | 5, 11* | ↑ 4-fold (2.8, 6.1X) ↑ 38-fold (28, 56X) | ↑ 2.5-fold (1.9, 3.4X) ↑ 16-fold (13, 20X) | ↑ 6-fold (3.5, 18.3X) ↑ 181-fold (ND)
Sildenafil | 100, single dose | 500 twice daily, 8 d | 28 | ↑ 11-fold | ↑ 4-fold | ND
Simeprevir | 200 mg qd, 7 d | 100 mg bid, 15 d | 12 | ↑ 618% (463%-815%)^8 | ↑370% (284%-476%)^8 | ↑1335% (929%-1901%)^8
Sulfamethoxazole^3 | 800, single dose | 500 q12h, 12 d | 15 | ↓ 20% (16, 23%) | ↔ | ND
Tadalafil | 20 mg, single dose | 200 mg q12h |  | ↑ 124% | ↔ | ND
Theophylline | 3 mg/kg q8h, 15 d | 500 q12h, 10 d | 13, 11* | ↓ 43% (42, 45%) | ↓ 32% (29, 34%) | ↓ 57% (55, 59%)
Trazodone | 50 mg, single dose | 200 mg q12h, 4 doses | 10 | ↑ 2.4-fold | ↑ 34%
Trimethoprim^3 | 160, single dose | 500 q12h, 12 d | 15 | ↑ 20% (3, 43%) | ↔ | ND
Vardenafil | 5 mg | 600 q12h |  | ↑ 49-fold | ↑ 13-fold | ND
Voriconazole | 400 q12h, 1 d; then 200 q12h, 8 d | 400 q12h, 9 d |  | ↓ 82% | ↓ 66%
 | 400 q12h, 1 d; then 200 q12h, 8 d | 100 q12h, 9 d |  | ↓ 39% | ↓ 24%
Warfarin S-Warfarin R-Warfarin | 5, single dose | 400 q12h, 12d | 12 | ↑ 9% (-17, 44%)^4 ↓ 33% (-38, -27%)^4 | ↓ 9% (-16, -2%)^4 ↔ | ND ND
Zidovudine | 200 q8h, 4 d | 300 q6h, 4 d | 9 | ↓ 25% (15, 34%) | ↓ 27% (4, 45%) | ND
ND=not determined
1 Ritonavir and indinavir were co-administered for 15 days; Day 14 doses were administered after a 15%-fat breakfast (757 Kcal) and 9%-fat evening snack (236 Kcal), and Day 15 doses were administered after a 15%-fat breakfast (757 Kcal) and 32%-fat dinner (815 Kcal). Indinavir Cmin was also increased 4-fold. Effects were assessed relative to an indinavir 800 mg q8h regimen under fasting conditions.
2 Effects were assessed on a dose-normalized comparison to a methadone 20 mg single dose.
3 Sulfamethoxazole and trimethoprim taken as single combination tablet.
4 90% CI presented for R- and S-warfarin AUC and Cmax ratios.
5 This significant increase in plasma fluticasone propionate exposure resulted in a significant decrease (86%) in plasma cortisol AUC.
6 For the reference arm: N=14 for Cmax and AUC(0-inf), and for the test arm: N=13 for Cmax and N=4 for AUC(0-inf).
7 90% CI presented for rivaroxaban
8 90% CI presented for simeprevir (change in exposure presented as percentage increase)
↑ Indicates increase, ↓ indicates decrease, ↔ indicates no change.
* Parallel group design; entries are subjects receiving combination and control regimens, respectively.

12.4 Microbiology

Mechanism of Action

Ritonavir is a peptidomimetic inhibitor of the HIV-1 protease. Inhibition of HIV protease renders the enzyme incapable of processing the Gag-Pol polyprotein precursor which leads to production of non-infectious immature HIV particles.

Antiviral Activity in Cell Culture

The activity of ritonavir was assessed in acutely infected lymphoblastoid cell lines and in peripheral blood lymphocytes. The concentration of drug that inhibits 50% (EC50) value of viral replication ranged from 3.8 to 153 nM depending upon the HIV-1 isolate and the cells employed. The average EC50 value for low passage clinical isolates was 22 nM (n = 13). In MT4 cells, ritonavir demonstrated additive effects against HIV-1 in combination with either didanosine (ddI) or zidovudine (ZDV). Studies which measured cytotoxicity of ritonavir on several cell lines showed that greater than 20 microM was required to inhibit cellular growth by 50% resulting in a cell culture therapeutic index of at least 1000.

Resistance

HIV-1 isolates with reduced susceptibility to ritonavir have been selected in cell culture. Genotypic analysis of these isolates showed mutations in the HIV-1 protease gene leading to amino acid substitutions I84V, V82F, A71V, and M46I. Phenotypic (n = 18) and genotypic (n = 48) changes in HIV-1 isolates from selected patients treated with ritonavir were monitored in phase I/II trials over a period of 3 to 32 weeks. Substitutions associated with the HIV–1 viral protease in isolates obtained from 43 patients appeared to occur in a stepwise and ordered fashion at positions V82A/F/T/S, I54V, A71V/T, and I36L, followed by combinations of substitutions at an additional 5 specific amino acid positions (M46I/L, K20R, I84V, L33F and L90M). Of 18 patients for whom both phenotypic and genotypic analysis were performed on free virus isolated from plasma, 12 showed reduced susceptibility to ritonavir in cell culture. All 18 patients possessed one or more substitutions in the viral protease gene. The V82A/F substitution appeared to be necessary but not sufficient to confer phenotypic resistance. Phenotypic resistance was defined as a greater than or equal to 5-fold decrease in viral sensitivity in cell culture from baseline.

Cross-Resistance to Other Antiretrovirals

Among protease inhibitors variable cross-resistance has been recognized. Serial HIV-1 isolates obtained from six patients during ritonavir therapy showed a decrease in ritonavir susceptibility in cell culture but did not demonstrate a concordant decrease in susceptibility to saquinavir in cell culture when compared to matched baseline isolates. However, isolates from two of these patients demonstrated decreased susceptibility to indinavir in cell culture (8-fold). Isolates from 5 patients were also tested for cross-resistance to amprenavir and nelfinavir; isolates from 3 patients had a decrease in susceptibility to nelfinavir (6- to 14-fold), and none to amprenavir. Cross-resistance between ritonavir and reverse transcriptase inhibitors is unlikely because of the different enzyme targets involved. One ZDV-resistant HIV-1 isolate tested in cell culture retained full susceptibility to ritonavir.

13 NONCLINICAL TOXICOLOGY

13.1 Carcinogenesis, Mutagenesis, Impairment of Fertility

Carcinogenesis

Carcinogenicity studies in mice and rats have been carried out on ritonavir. In male mice, at levels of 50, 100 or 200 mg per kg per day, there was a dose dependent increase in the incidence of both adenomas and combined adenomas and carcinomas in the liver. Based on AUC measurements, the exposure at the high dose was approximately 0.3-fold for males that of the exposure in humans with the recommended therapeutic dose (600 mg twice-daily). There were no carcinogenic effects seen in females at the dosages tested. The exposure at the high dose was approximately 0.6-fold for the females that of the exposure in humans. In rats dosed at levels of 7, 15 or 30 mg per kg per day there were no carcinogenic effects. In this study, the exposure at the high dose was approximately 6% that of the exposure in humans with the recommended therapeutic dose. Based on the exposures achieved in the animal studies, the significance of the observed effects is not known.

Mutagenesis

However, ritonavir was found to be negative for mutagenic or clastogenic activity in a battery of in vitro and in vivo assays including the Ames bacterial reverse mutation assay using S. typhimurium and E. coli, the mouse lymphoma assay, the mouse micronucleus test and chromosomal aberration assays in human lymphocytes.

Impairment of Fertility

Ritonavir produced no effects on fertility in rats at drug exposures approximately 40% (male) and 60% (female) of that achieved with the proposed therapeutic dose. Higher dosages were not feasible due to hepatic toxicity.

14 CLINICAL STUDIES

The activity of NORVIR as monotherapy or in combination with nucleoside reverse transcriptase inhibitors has been evaluated in 1446 patients enrolled in two double-blind, randomized trials.

14.1 Advanced Patients with Prior Antiretroviral Therapy

Study 247 was a randomized, double-blind trial (with open-label follow-up) conducted in HIV-infected patients with at least nine months of prior antiretroviral therapy and baseline CD4 cell counts less than or equal to 100 cells per μL. NORVIR 600 mg twice-daily or placebo was added to each patient's baseline antiretroviral therapy regimen, which could have consisted of up to two approved antiretroviral agents. The study accrued 1,090 patients, with mean baseline CD4 cell count at study entry of 32 cells per μL. After the clinical benefit of NORVIR therapy was demonstrated, all patients were eligible to switch to open-label NORVIR for the duration of the follow-up period. Median duration of double-blind therapy with NORVIR and placebo was 6 months. The median duration of follow-up through the end of the open-label phase was 13.5 months for patients randomized to NORVIR and 14 months for patients randomized to placebo.

The cumulative incidence of clinical disease progression or death during the double-blind phase of Study 247 was 26% for patients initially randomized to NORVIR compared to 42% for patients initially randomized to placebo. This difference in rates was statistically significant.

Cumulative mortality through the end of the open-label follow-up phase for patients enrolled in Study 247 was 18% (99/543) for patients initially randomized to NORVIR compared to 26% (142/547) for patients initially randomized to placebo. This difference in rates was statistically significant. However, since the analysis at the end of the open-label phase includes patients in the placebo arm who were switched from placebo to NORVIR therapy, the survival benefit of NORVIR cannot be precisely estimated.

During the double-blind phase of Study 247, CD4 cell counts increases from baseline for patients randomized to NORVIR at Week 2 and Week 4 were observed. From Week 4 and through Week 24, mean CD4 cell counts for patients randomized to NORVIR appeared to plateau. In contrast, there was no apparent change in mean CD4 cell counts for patients randomized to placebo at any visit between baseline and Week 24 of the double-blind phase of Study 247.

14.2 Patients without Prior Antiretroviral Therapy

In Study 245, 356 antiretroviral-naive HIV-infected patients (mean baseline CD4 = 364 cells per μL) were randomized to receive either NORVIR 600 mg twice-daily, zidovudine 200 mg three-times-daily, or a combination of these drugs.

During the double-blind phase of study 245, greater mean CD4 cell count increases were observed from baseline to Week 12 in the NORVIR-containing arms compared to the zidovudine arms. Mean CD4 cell count changes subsequently appeared to plateau through Week 24 in the NORVIR arm, whereas mean CD4 cell counts gradually diminished through Week 24 in the zidovudine and NORVIR plus zidovudine arms.

Greater mean reductions in plasma HIV-1 RNA levels were observed from baseline to Week 2 for the NORVIR-containing arms compared to the zidovudine arm. After Week 2 and through Week 24, mean plasma HIV-1 RNA levels either remained stable in the NORVIR and zidovudine arms or gradually rebounded toward baseline in the NORVIR plus zidovudine arm.

15 REFERENCES

1. Sewester CS. Calculations. In: Drug Facts and Comparisons. St. Louis, MO: J.B. Lippincott Co; January, 1997:xix.

16 HOW SUPPLIED/STORAGE AND HANDLING

The package sizes, strengths, and storage and handling recommendations for NORVIR (ritonavir) tablets and oral powder are shown in the table below.

 | NORVIR Tablets, 100 mg Ritonavir | NORVIR Oral Powder, 100 mg Packet
Presentation | White film-coated ovaloid tablets debossed with the "a" logo and the code NK | beige/pale yellow to yellow powder, in packets containing 100 mg of ritonavir
 | White film-coated ovaloid tablets debossed with “NK” on one side providing 100 mg ritonavir.
Packaging Size | Bottles containing 30 tablets | 30 foil/laminate, child-resistant packets per carton
NDC Number | 0074-3333-30 | 0074-3399-30
 | 0074-2340-30
Recommended Storage | Store at or below 30°C (86°F). Exposure to temperatures up to 50°C (122°F) for seven days permitted. Dispense in original container or USP equivalent tight container (60 mL or less). For patient use: exposure of this product to high humidity outside the original or USP equivalent tight container (60 mL or less) for longer than 2 weeks is not recommended. | Store at or below 30°C (86°F)

17 PATIENT COUNSELING INFORMATION

Advise the patient to read the FDA-approved patient labeling (Patient Information and Instructions for Use)

General Administration Information [see Dosage and Administration (2)]:

- Advise patients and caregivers to pay special attention to accurate preparation and administration of their dose to minimize the risk of accidental overdose or underdose of NORVIR.
- For Norvir oral powder, advise patients or caregivers to read and follow the Instructions for Use for preparing the correct dose.
- Advise caregivers to inform their healthcare provider if their child’s weight changes in order to make sure that the child’s NORVIR dose is adjusted as needed.
- Advise patients to take NORVIR with meals.
- For adult patients taking NORVIR tablets, the maximum dose of 600 mg twice daily by mouth with meals should not be exceeded.
- Advise patients to remain under the care of a physician while using NORVIR and to take NORVIR and other concomitant antiretroviral therapy every day as prescribed. NORVIR must always be used in combination with other antiretroviral drugs. Advise patients not to alter the dose or discontinue therapy without consulting with their healthcare provider. If a dose of NORVIR is missed patients should take the dose as soon as possible and then return to their normal schedule. However, if a dose is skipped the patient should not double the next dose.
- Continued NORVIR therapy at a dose of 600 mg twice daily following loss of viral suppression may increase the likelihood of cross-resistance to other protease inhibitors.
- NORVIR is not a cure for HIV-1 infection and patients may continue to experience illnesses associated with HIV-1 infection, including opportunistic infections. Patients should remain under the care of a physician when using NORVIR.

Drug Interactions

- NORVIR may interact with some drugs; therefore, patients should be advised to report to their doctor the use of any other prescription, non-prescription medication or herbal products, particularly St. John's Wort.
- Instruct patients receiving combined hormonal contraception to use an effective alternative contraceptive method or an additional barrier method during therapy with NORVIR because hormonal levels may decrease [see Drug Interactions (7.2), Use in Specific Populations (8.3)].

Hepatotoxicity

Pre-existing liver disease including Hepatitis B or C can worsen with use of NORVIR. This can be seen as worsening of transaminase elevations or hepatic decompensation. Advise patients that their liver function tests will need to be monitored closely especially during the first several months of NORVIR treatment and that they should notify their healthcare provider if they develop the signs and symptoms of worsening liver disease including loss of appetite, abdominal pain, jaundice, and itchy skin [see Warnings and Precautions (5.2)].

Pancreatitis

Pancreatitis, including some fatalities, has been observed in patients receiving NORVIR therapy. Advise patients to notify their healthcare provider of signs and symptoms (nausea, vomiting, and abdominal pain) that might be suggestive of pancreatitis [see Warnings and Precautions (5.3)].

Allergic Reactions/Hypersensitivity

Skin rashes ranging in severity from mild to Stevens-Johnson syndrome have been reported in patients receiving NORVIR. Advise patients to contact their healthcare provider if they develop a rash while taking NORVIR [see Warnings and Precautions (5.4)].

PR Interval Prolongation

NORVIR may produce changes in the electrocardiogram (e.g., PR prolongation). Advise patients to consult their healthcare provider if they experience symptoms such as dizziness, lightheadedness, abnormal heart rhythm or loss of consciousness [see Warnings and Precautions (5.5)].

Lipid Disorders

Advise patients that treatment with NORVIR therapy can result in substantial increases in the concentration of total cholesterol and triglycerides [see Warnings and Precautions (5.6)].

Diabetes Mellitus/Hyperglycemia

Advise patients that new onset of diabetes or exacerbation of pre-existing diabetes mellitus, and hyperglycemia have been reported and to notify their healthcare provider if they develop the signs and symptoms of diabetes mellitus including frequent urination, excessive thirst, extreme hunger or unusual weight loss and/or an increased blood sugar while on NORVIR as they may require a change in their diabetes treatment or new treatment [see Warnings and Precautions (5.7)].

Immune Reconstitution Syndrome

Advise patients that immune reconstitution syndrome has been reported in HIV-infected patients treated with combination antiretroviral therapy, including NORVIR [see Warnings and Precautions (5.8)].

Fat Redistribution

Advise patients that redistribution or accumulation of body fat may occur in patients receiving antiretroviral therapy and that the cause and long term health effects of these conditions are not known at this time [see Warnings and Precautions (5.9)].

Patients with Hemophilia

Advise patients with hemophilia that they may experience increased bleeding when treated with protease inhibitors such as NORVIR [see Warnings and Precautions (5.10)].

Pregnancy Exposure Registry

Inform patients that there is an antiretroviral pregnancy registry that monitors fetal outcomes of pregnant women exposed to NORVIR [see Use in Specific Populations (8.1)].

Lactation

Instruct women with HIV-1 infection not to breastfeed because HIV-1 can be passed to the baby in breast milk [see Use in Specific Populations (8.2)].

NORVIR tablets are manufactured by:
AbbVie Inc.
North Chicago, IL 60064 USA

NORVIR oral powder is manufactured for:
AbbVie Inc.
North Chicago, IL 60064 USA

© 2024 AbbVie Inc. All rights reserved.
20086922 R1

Patient Information

NORVIR®
(NOR-VEER)
(ritonavir)
Tablets

NORVIR®
(NOR-VEER)
(ritonavir)
Oral Powder

What is the most important information I should know about NORVIR?

- NORVIR can interact with other medicines and cause serious side effects. It is important to know the medicines that should not be taken with NORVIR. See the section “Who should not take NORVIR?”

What is NORVIR?

- NORVIR tablets are prescription medicines that are used with other antiviral medicines to treat people with human immunodeficiency virus (HIV-1) infection.
- NORVIR oral powder is a prescription medicine that is used with other antiviral medicines to treat children with HIV-1 infection.

HIV-1 is the virus that causes AIDS (Acquired Immune Deficiency Syndrome).

Do not take NORVIR if you or your child:
○ are allergic to ritonavir or any of the ingredients in NORVIR. See the end of this leaflet for a complete list of ingredients in NORVIR.
○ If you take any of the following medicines:
○ alfuzosin
○ apalutamide
○ ranolazine
○ dronedarone
○ colchicine, if you have kidney or liver problems.
○ lurasidone
○ pimozide
○ amiodarone
○ ergot-containing medicines including:
○ dihydroergotamine mesylate
○ ergotamine tartrate
○ methylergonovine maleate
○ cisapride
○ flecainide
○ lovastatin
○ simvastatin
○ lomitapide
○ sildenafil (REVATIO®) only when used for treating the lung problem, pulmonary arterial hypertension (PAH)
○ triazolam
○ midazolam when taken by mouth
○ propafenone
○ quinidine
○ St. John’s Wort (Hypericum perforatum) or a product that contains St. John’s wort
○ voriconazole if your NORVIR dose is 400 mg every 12 hours or greater
Serious problems can happen if you or your child takes any of these medicines with NORVIR.

Before taking NORVIR, tell your healthcare provider about all of your medical conditions, including if you or your child:

- have liver problems, including Hepatitis B or Hepatitis C
- have heart problems
- have high blood sugar (diabetes)
- have bleeding problems or hemophilia
- are pregnant or plan to become pregnant.
  ○ NORVIR may reduce how well hormonal birth control works. Females who may become pregnant should use another effective form of birth control or an additional barrier method of birth control during treatment with NORVIR.
  ○ Pregnancy Registry: There is a pregnancy registry for women who take antiviral medicines during pregnancy. The purpose of the registry is to collect information about the health of you and your baby. Talk to your healthcare provider about how you can take part in this registry.
- are breastfeeding or plan to breastfeed. Do not breastfeed if you take NORVIR.
  ○ You should not breastfeed if you have HIV-1 because of the risk of passing HIV-1 to your baby.
  ○ NORVIR may pass into your breastmilk.
  ○ Talk to your healthcare provider about the best way to feed your baby.

Tell your healthcare provider about all the medicines you take including prescription and over-the-counter medicines, vitamins, and herbal supplements. Some medicines interact with NORVIR. Keep a list of your medicines to show our healthcare provider and pharmacist.

- You can ask your healthcare provider or pharmacist for a list of medicines that interact with NORVIR.
- Do not start taking a new medicine without telling your healthcare provider. Your healthcare provider can tell you if it is safe to take NORVIR with other medicines.

How should I take NORVIR?
See the detailed Instructions for Use for information about how to give or take a dose of NORVIR oral powder.

- Take NORVIR exactly as your healthcare provider tells you to take it.
- You should stay under a healthcare provider's care during treatment with NORVIR. Do not change your dose of NORVIR or stop your treatment without talking with your healthcare provider first.
- If your child is taking NORVIR, your child’s healthcare provider will decide the right dose based on your child's height and weight. Tell your healthcare provider if your child’s weight changes. If your child does not tolerate NORVIR oral powder, ask your child’s healthcare provider for advice.
- Swallow NORVIR tablets whole. Do not chew, break, or crush tablets before swallowing. If you cannot swallow NORVIR tablets whole, tell your healthcare provider. You may need a different medicine.
- Take NORVIR with meals.
- Do not run out of NORVIR. Get your NORVIR prescription refilled from your healthcare provider or pharmacy before you run out.
- If you miss a dose of NORVIR, take it as soon as possible and then take your next scheduled dose at its regular time. If it is almost time for your next dose, wait and take the next dose at the regular time. Do not double the next dose.
- If you take too much NORVIR, call your local poison control center or go to the nearest hospital emergency room right away.

What are the possible side effects of NORVIR?
NORVIR can cause serious side effects including:

- See “What is the most important information I should know about NORVIR?”
- Liver problems. Some people taking NORVIR in combination with other antiviral medicines have developed liver problems which may be life-threatening. Your healthcare provider should do regular blood tests during your combination treatment with NORVIR. If you have chronic hepatitis B or C infection, your healthcare provider should check your blood tests more often because you have an increased chance of developing liver problems. Tell your healthcare provider right away if you get any of the following signs and symptoms of liver problems:

○ loss of appetite
○ pain or tenderness on your right side below your ribs

○ yellowing of your skin or whites of your eyes
○ itchy skin

- Inflammation of your pancreas (pancreatitis). NORVIR can cause serious pancreas problems, which may lead to death. Tell your healthcare provider right away if you have signs or symptoms of pancreatitis such as:

○ nausea
○ stomach (abdomen) pain

○ vomiting

- Allergic reactions. Sometimes these allergic reactions can become severe and require treatment in a hospital. Call your healthcare provider right away if you develop a rash. Stop taking NORVIR and get medical help right away if you have any of the following symptoms of a severe allergic reaction:

○ trouble breathing
○ wheezing
○ dizziness or fainting
○ throat tightness or hoarseness
○ fast heartbeat or pounding in your chest (tachycardia)

○ sweating
○ swelling of your face, lips or tongue
○ muscle or joint pain
○ blisters or skin lesions
○ mouth sores or ulcers

Changes in the electrical activity of your heart called PR prolongation. PR prolongation can cause irregular heartbeats. Tell your healthcare provider right away if you have symptoms such as:

○ dizziness
○ lightheadedness

○ feel faint or pass out
○ abnormal heart beat

- Increase in cholesterol and triglyceride levels. Treatment with NORVIR may increase your blood levels of cholesterol and triglycerides. Your healthcare provider should do blood tests before you start your treatment with NORVIR and regularly to check for an increase in your cholesterol and triglycerides levels.
- Diabetes and high blood sugar (hyperglycemia). Some people who take protease inhibitors including NORVIR can get high blood sugar, develop diabetes, or your diabetes can get worse. Tell your healthcare provider if you notice an increase in thirst or urinate often during treatment with NORVIR.
- Changes in your immune system (Immune Reconstitution Syndrome) can happen when you start taking HIV-1 medicines. Your immune system may get stronger and begin to fight infections that have been hidden in your body for a long time. Call your healthcare provider right away if you start having new symptoms after starting your HIV-1 medicine.
- Change in body fat can happen in some people who taking HIV-1 medicines. These changes may include an increased amount of fat in the upper back and neck (“buffalo hump”), breast, and around the middle part of your body (trunk). Loss of fat from the legs, arms, and face may also happen. The exact cause and long-term health effects of these conditions are not known.
- Increased bleeding for hemophiliacs. Some people with hemophilia have increased bleeding with protease inhibitors including NORVIR.
- Kidney stones

The most common side effects of NORVIR include:

- diarrhea
- nausea
- vomiting
- upper and lower stomach (abdominal) pain

- tingling feeling or numbness in hands or feet or around the lips
- rash
- feeling weak or tired

These are not all of the possible side effects of NORVIR. Call your doctor for medical advice about side effects. You may report side effects to FDA at 1-800-FDA-1088.

How should I store NORVIR?

- Store NORVIR tablets in the original container given to you by the pharmacist.
- Use NORVIR tablets and NORVIR oral powder by the expiration date.

Store NORVIR tablets:

- Store below 30°C (86°F). Exposure to temperatures up to 50°C (122°F) for seven days permitted.
- Exposure to high humidity outside the original container for longer than 2 weeks is not recommended.

Store NORVIR oral powder:

- At or below 30°C (86°F).

Keep NORVIR and all medicines out of the reach of children.

General information about the safe and effective use of NORVIR
Medicines are sometimes prescribed for purposes other than those listed in a Patient Information Leaflet. Do not use NORVIR for a condition for which it was not prescribed. Do not give NORVIR to other people, even if they have the same symptoms that you have. It may harm them. You can ask your pharmacist or healthcare provider for information about NORVIR that is written for healthcare professionals.

What are the ingredients in NORVIR?
Active ingredient: ritonavir
Inactive ingredients:
NORVIR tablet: copovidone, anhydrous dibasic calcium phosphate, sorbitan monolaurate, colloidal silicon dioxide, and sodium stearyl fumarate. The film coating contains: hypromellose, titanium dioxide, polyethylene glycol 400, hydroxypropyl cellulose, talc, polyethylene glycol 3350, colloidal silicon dioxide, and polysorbate 80.
NORVIR oral powder: copovidone, sorbitan monolaurate, and colloidal silicon dioxide.
NORVIR tablets are manufactured by: AbbVie Inc., North Chicago, IL 60064 USA. NORVIR oral powder is manufactured for: AbbVie Inc., North Chicago, IL 60064 USA. For more information, call 1-800-633-9110. The brands listed are trademarks of their respective owners and are not trademarks of AbbVie Inc. The makers of these brands are not affiliated with and do not endorse AbbVie Inc. or its products. © 2024 AbbVie Inc. All rights reserved.

This Patient Information has been approved by the U.S. Food and Drug Administration.
20086922 R1

Revised: July 2024

Instructions for Use
NORVIR®
(ritonavir)
oral powder

Read these Instructions for Use before you give or take a dose of NORVIR oral powder for the first time and every time you get a new prescription. There may be new information. Talk to your healthcare provider if you have any questions.

Important information

- Your healthcare provider will tell you your dose of NORVIR oral powder and how many packets you will need.
- Each packet contains 100 mg of NORVIR oral powder.
- When you receive your NORVIR oral powder prescription at the pharmacy, check to make sure that the carton is not damaged and that the packets are not opened.
- Check that the expiration date on the carton and packet has not passed.
- Make sure you have enough packets of NORVIR oral powder to give a full dose. Call your healthcare provider if you need more NORVIR oral powder. Do not run out of your medicine.
- NORVIR oral powder can be prepared with either food or liquid. This Instructions for Use is for preparing the dose with food.
- The food can be replaced with a liquid and the same steps can be followed for preparing a dose.
- If your healthcare provider tells you to give NORVIR oral powder through a feeding tube, use water to mix NORVIR oral powder. Follow your healthcare provider’s instructions to give the mixture through a feeding tube.
- Be sure to give or take the entire prepared dose of NORVIR oral powder within 2 hours of preparing the dose.

For more information about NORVIR oral powder see the Patient Information section of the Prescribing Information.

Items included in the NORVIR oral powder carton

Figure A

Gather items to prepare your dose

If your dose is 100 mg or 200 mg: You will need 1 packet of NORVIR oral powder for 100 mg and 2 packets of NORVIR oral powder for 200 mg.

Note: If your healthcare provider prescribes a dose of NORVIR oral powder that is not 100 mg or 200 mg, your healthcare provider should tell you how to prepare your dose. Be sure to prepare your dose exactly as your healthcare provider tells you.

You will also need the following items to prepare your dose of NORVIR oral powder with food (not included in the NORVIR oral powder carton):

- Soft food such as applesauce or vanilla pudding
- Spoon
- Small cup or bowl

Figure B

If you are preparing a dose of NORVIR oral powder in liquid, you will also need the following items (not included in your NORVIR oral powder carton):

- Drinking glass with 4 oz. of drinking water, infant formula or chocolate milk
- Spoon (teaspoon or larger)

Figure C

The instructions below show the dose being prepared with food, but if you are using liquid you can swap the food for a liquid.

Prepare your dose

Step 1: Place your supplies on a clean, flat surface, like a table.
Check to make sure your small cup or bowl and spoon are clean and dry.

Step 2: Check the prescription label on the carton for the number of packets you need to prepare a dose.
Take the prescribed number of packets out of the carton. For example, remove 1 packet if your dose is 100 mg or 2 packets if your dose is 200 mg.

Figure D

Step 3: Put a spoonful or more of soft food into the small cup or bowl.

Figure E

Step 4: Tap the packet(s) to move all the powder to the bottom of the packet.
Completely tear or cut off the top of the packet and make sure the packet is fully open.

Figure F

Step 5: Pour all of the powder from the packet(s) onto the soft food.
Look inside the packet(s) to make sure there is no powder left inside. If there is powder left inside, hold the open end of the packet over your small cup or bowl and tap the packet(s) again to get all of the powder out.
Note: To make sure a full dose of NORVIR is given, it is important not to spill any powder and that there is no powder left in the packet(s).

Figure G

Step 6: Use the spoon to mix the powder and soft food well.
Note: If mixing NORVIR oral powder with a liquid, the mixture may look cloudy. This is okay.

Figure H

Step 7: Give or take the mixture.
Be sure that all of the mixture is taken.
If there is any powder left in the small cup, bowl, or spoon, add more soft food to the powder and mix. Then give or take the mixture.
If there is any powder left in the drinking glass, add more liquid to the powder and mix. Then give or take the mixture.
Note: The mixture must be given within 2 hours of mixing with food or liquid. If not given within 2 hours of mixing, discard (throw away) the mixture and prepare a new dose.
If only part of the dose has been taken or given within the 2 hours, follow up with your healthcare provider.

Figure I

Step 8: Put the empty packet(s) in the trash.
Hand wash the spoon, small cup or bowl, or drinking glass in warm water and soap.
Rinse the spoon, small cup or bowl, or drinking glass with warm water and allow to air dry.
Wash and dry the area used to prepare the NORVIR mixture.
Wash and dry your hands.

This Instructions for Use has been approved by the U.S. Food and Drug Administration.

Manufactured by: NORVIR Oral Powder is manufactured for: AbbVie Inc., North Chicago, IL 60064 USA.

Issued: September 2017

430135

PACKAGE LABEL

NDC 0074-3333-30

No Image Available

PACKAGE LABEL

NDC 0074-1940-63

No Image Available

PACKAGE LABEL

NDC 0074-3399-30

Norvir®

(ritonavir) Oral Powder 100 mg

For Oral Use

ALERT: Find out about medicines that should NOT be taken with Norvir.

Note to Pharmacist: Do not cover ALERT box with pharmacy label.

Package insert is provided with tear-off patient information.

30 single-use foil packets

Rx only abbvie

PACKAGE LABEL

NDC 0074-2340-30

Norvir®

Ritonavir Tablets 100 mg 30 Tablets

Attention Pharmacists and Patients: Tablet formulation. Store at room temperature (see side panel). Take NORVIR with meals.

ALERT: Find out about medicines that should NOT be taken with NORVIR.

Note to Pharmacist: Do not cover ALERT box with pharmacy label.

Package insert is provided with tear-off patient information.

Rx only abbvie